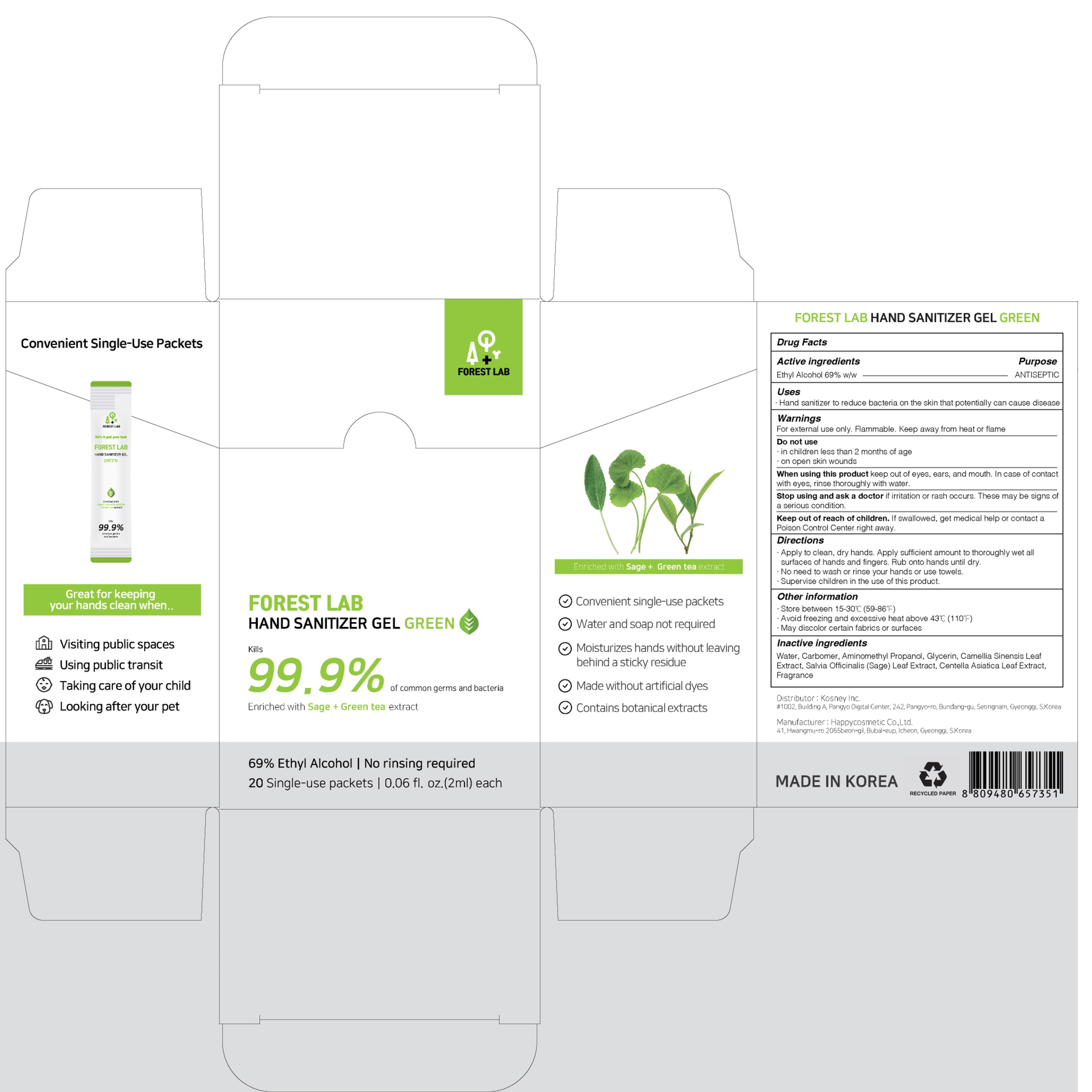 DRUG LABEL: FOREST LAB HAND SANITIZER GREEN
NDC: 79704-020 | Form: GEL
Manufacturer: Kosney Inc.
Category: otc | Type: HUMAN OTC DRUG LABEL
Date: 20200722

ACTIVE INGREDIENTS: ALCOHOL 69 g/100 mL
INACTIVE INGREDIENTS: Water; CARBOMER HOMOPOLYMER, UNSPECIFIED TYPE; AminomethylPropanol; Glycerin; GREEN TEA LEAF; SAGE; CENTELLA ASIATICA LEAF

ACTIVE INGREDIENT

Ethyl Alcohol 69% w/w

INACTIVE INGREDIENTS

Water, Carbomer, Aminomethyl Propanol, Glycerin, Camellia Sinensis Leaf Extract, Salvia Officinalis (Sage) Leaf Extract, Centella Asiatica Leaf Extract, Fragrance

PURPOSE

ANTISEPTIC

WARNINGS

For external use only. Flammable. Keep away from heat or flame
--------------------------------------------------------------------------------------------------------
Do not use
• in children less than 2 months of age
• on open skin wounds
--------------------------------------------------------------------------------------------------------
When using this product keep out of eyes, ears, and mouth. In case of contact with eyes, rinse thoroughly with water.
--------------------------------------------------------------------------------------------------------
Stop use and ask a doctor if irritation or rash occurs. These may be signs of a serious condition.

KEEP OUT OF REACH OF CHILDREN

If swallowed, get medical help or contact a Poison Control Center right away.

Uses

• Hand sanitizer to reduce bacteria on the skin that potentially can cause disease

Directions

• Apply to clean, dry hands. Apply sufficient amount to thoroughly wet all surfaces of hands and fingers. Rub onto hands until dry.
• No need to wash or rinse hands or use towels
• Supervise children in the use of this product.

Other Information

• Store between 15-30℃ (59-86℉)
• Avoid freezing and excessive heat above 43℃ (110℉)
• May discolor certain fabrics or surfaces